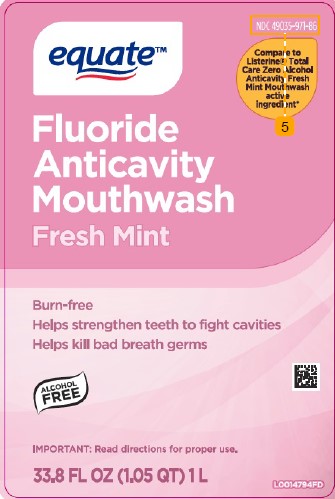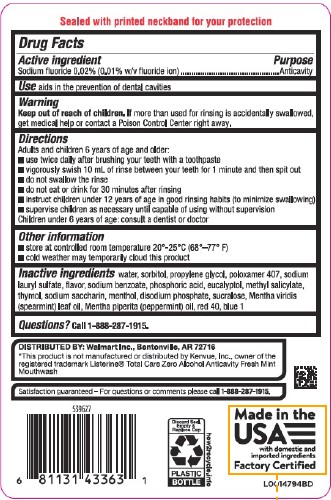 DRUG LABEL: Anticavity
NDC: 49035-971 | Form: RINSE
Manufacturer: Walmart Inc.
Category: otc | Type: HUMAN OTC DRUG LABEL
Date: 20260227

ACTIVE INGREDIENTS: SODIUM FLUORIDE 0.1 mg/1 mL
INACTIVE INGREDIENTS: SODIUM LAURYL SULFATE; SODIUM BENZOATE; PHOSPHORIC ACID; EUCALYPTOL; METHYL SALICYLATE; THYMOL; WATER; SORBITOL; PROPYLENE GLYCOL; POLOXAMER 407; SACCHARIN SODIUM; MENTHOL; SODIUM PHOSPHATE, DIBASIC, ANHYDROUS; SUCRALOSE; SPEARMINT OIL; PEPPERMINT OIL; FD&C RED NO. 40; FD&C BLUE NO. 1

Equate 971.001/1971AB
Burn-Free Fluoride Anti-Cavity Mouthwash

Tamper Evident Statement

Sealed with printed neckband for your protection.

active ingredients

Sodium fluoride 0.02% (0.01% w/v fluoride ion)

Purpose

Anticavity

Use

aids in the prevention of dental cavities

Warning

For this product

Keep out of reach of children.

If more than used for rinsing is accidentally swallowed, get medical help or contact a Poison Control Center right away.

Directions

Adults and children 6 years of age and older:

- use twice daily after brushing your teeth with a toothpaste
- vigorously swish 10 mL of rinse between your teeth for 1 minute and then spit out.
- do not swallow the rinse
- do not eat or drink for 30 minutes after rinsing
- instruct children under 12 years of age in good rinsing habits (to minimize swallowing)
- supervise children as necessary until capable of using without supervision

Children under 6 years of age: consult a dentist or doctor

Other information

- store at room temperature 20⁰ - 25⁰ C (68⁰ - 77⁰ F)
- cold weather may temporarily cloud this product

Inactive ingredients

water, sorbitol, propylene glycol, poloxamer 407, sodium lauryl sulfate, flavor, sodium benzoate, phosphoric acid, eucalyptol, methyl salicylate, thymol, sodium saccharin, menthol, disodium phosphate, sucralose, Mentha viridis (spearmint) leaf oil, Mentha piperita (peppermint) oil, red 40, blue 1

Questions?

Call 1-888-287-1915

Adverse reactions

Distributed by: Walmart Inc.,

Bentonville, AR 72716

Satisfaction guaranteed - For questions or comments please call 1-888-287-1915.

Discard Seal, Empty & Replace Cap

PLASTIC BOTTLE

how2recycle.info

Made in the USA with domestic and imported ingredients

Factory Certified

Disclaimer

*This product is not manufactured or distributed by Kenvue, Inc., owner of the registered trademark Listerine®Total Care Zero Alcohol Anticavity Fresh Mint Mouthwash.

PRINCIPAL DISPLAY PANEL

NDC 49035-971-86

equate™

Compare to Listerine® Total Care Zero Alcohol Anticavity Fresh Mint Mouthwash active ingredient*

Fluoride Anticavity Mouthwash

Fresh Mint

Burn-free

Helps strengthen teeth to fight cavities

Helps kill bad breath germs

ALCOHOL FREE

IMPORTANT: Read directions fo proper use.

33.8 FL OZ (1.05 QT) 1 L